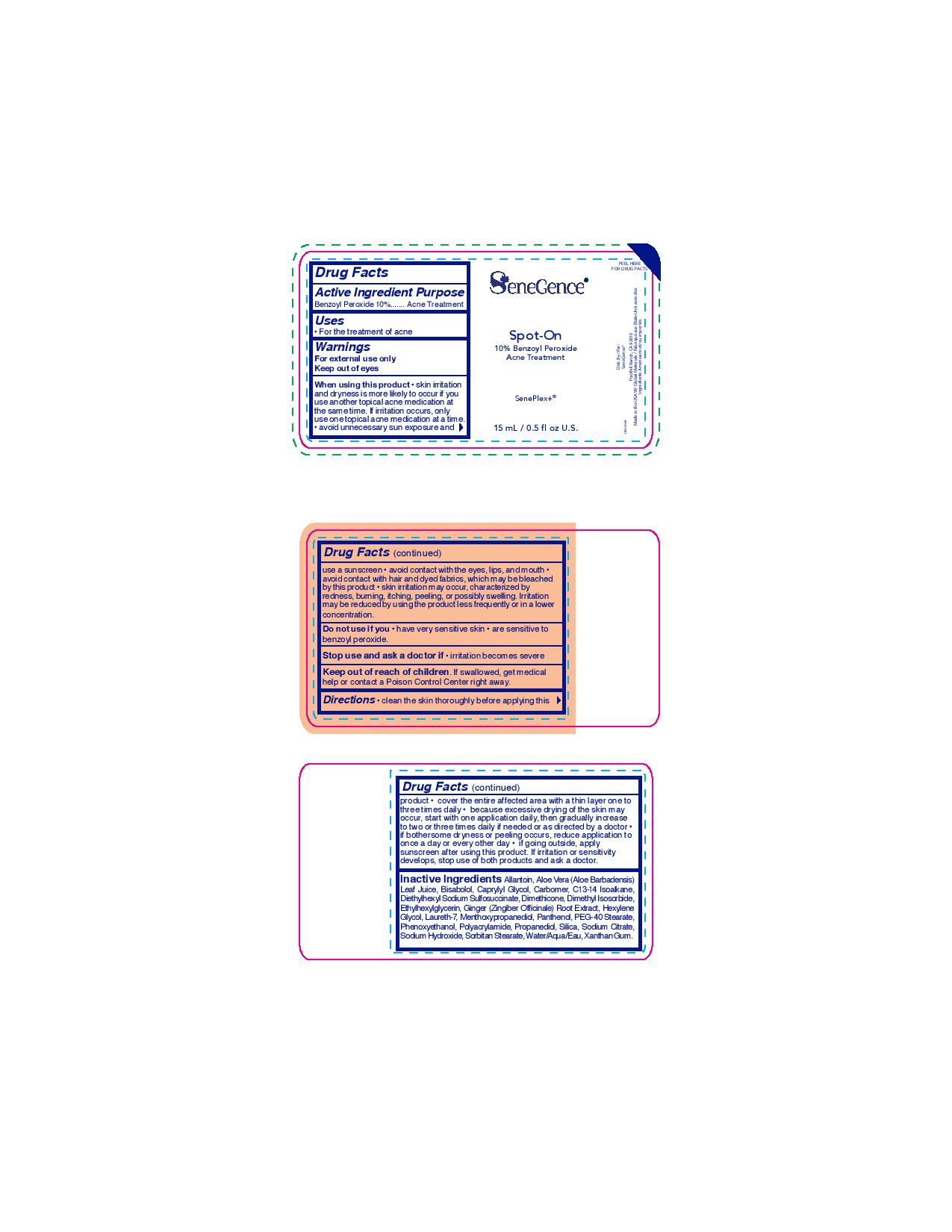 DRUG LABEL: Spot On Treatment
NDC: 72644-636 | Form: LOTION
Manufacturer: SGII, INC
Category: otc | Type: HUMAN OTC DRUG LABEL
Date: 20211207

ACTIVE INGREDIENTS: BENZOYL PEROXIDE 10 g/100 g
INACTIVE INGREDIENTS: PEG-40 STEARATE; SORBITAN MONOSTEARATE; DIMETHICONE; LAURETH-7; ALOE VERA LEAF; PROPANEDIOL; DIMETHYL ISOSORBIDE; SODIUM CITRATE; ALLANTOIN; LEVOMENOL; DOCUSATE SODIUM; PANTHENOL; CARBOMER HOMOPOLYMER, UNSPECIFIED TYPE; SODIUM HYDROXIDE; WATER; CAPRYLYL GLYCOL; ETHYLHEXYLGLYCERIN; GINGER; POLYACRYLAMIDE (10000 MW); C13-14 ISOPARAFFIN; 3-((L-MENTHYL)OXY)PROPANE-1,2-DIOL; PHENOXYETHANOL; XANTHAN GUM; SILICON DIOXIDE; HEXYLENE GLYCOL

Spot On Treatment

Active Ingredient

Benzoyl Peroxide 10%

Purpose

Acne Treatment

Uses

For the treatment of Acne

Warnings

For External Use Only

Keep Out Of Eyes

When using this product • Skin irritation and dryness is more likely to occur if you use another topical acne medication at the same time. If irritation occurs, only use one topical acne medication at a time. • avoid unnecessary sun exposure and use a sunscreen • avoid contact with the eyes, lips, and mouth • avoid contact with hair and dyed fabrics, which may be bleached by this product • skin irritation may occur, characterized by redness, burning, itching, peeling, or possibly swelling. Irritation may be reduced by using the product less frequently or in a lower concentration

Do not use if you • have very sensitive skin • are sensitive to benzoyl peroxide

Stop use and ask a doctor if • irritation becomes severe.

Keep out of reach of children. If swallowed, get medical help or contact a Poison Control Center right away.

Directions

•Clean the skin thoroughly before applying this product • cover the entire affected area with a thin layer one to three

times daily • because excessive drying of the skin may occur, start with one application daily, then gradually increase to two or three times daily if needed or as directed by a doctor • if bothersome dryness or peeling occurs, reduce application to once a day or every other day • if going outside, apply sunscreen after using this product. If irritation or sensitivity develops, stop use of both products and ask a doctor.

Inactive Ingredients

Allantoin, Aloe Vera (Aloe Barbadensis) Leaf Juice, Bisabolol, Caprylyl Glycol, Carbomer, C13-14 Isoalkane, Diethylhexyl Sodium Sulfosuccinate, Dimethicone, Dimethyl Isosorbide, Ethylhexylglycerin, Ginger (Zingiber Officinale) Root Extract, Hexylene Glycol, Laureth-7, Menthoxypropanediol, Panthenol, PEG-40 Stearate, Phenoxyethanol, Polyacrylamide, Propanediol, Silica, Sodium Citrate, Sodium Hydroxide, Sorbitan Stearate, Water/Aqua/Eau, Xanthan Gum.

PACKAGE LABEL

SeneGence

Spot-On

10% Benzoyl Peroxide

Acne Treatment

SenePlex+

15mL/0.5 fl oz U.S.